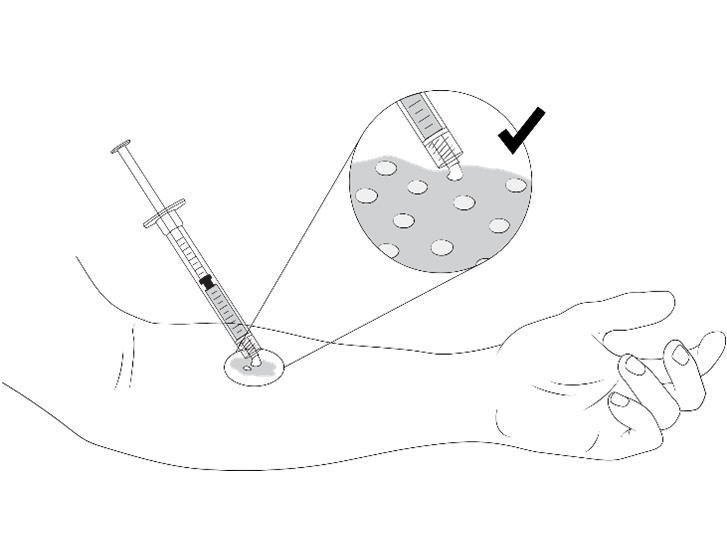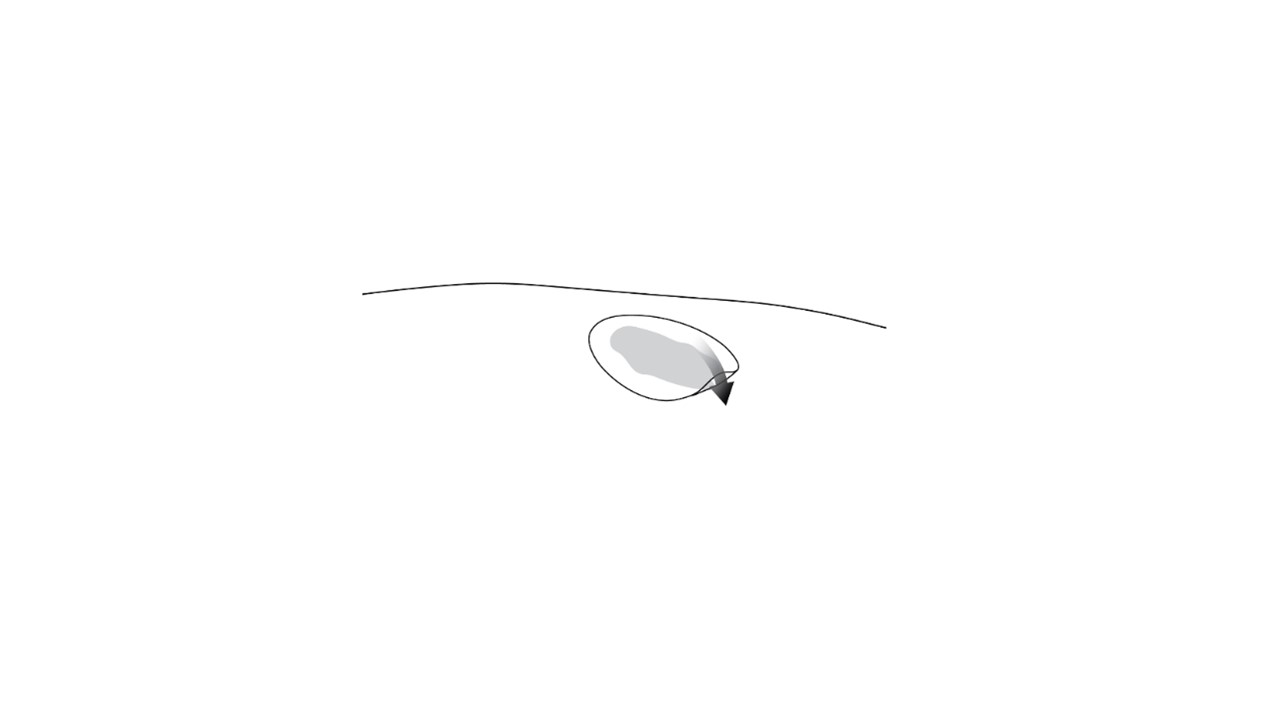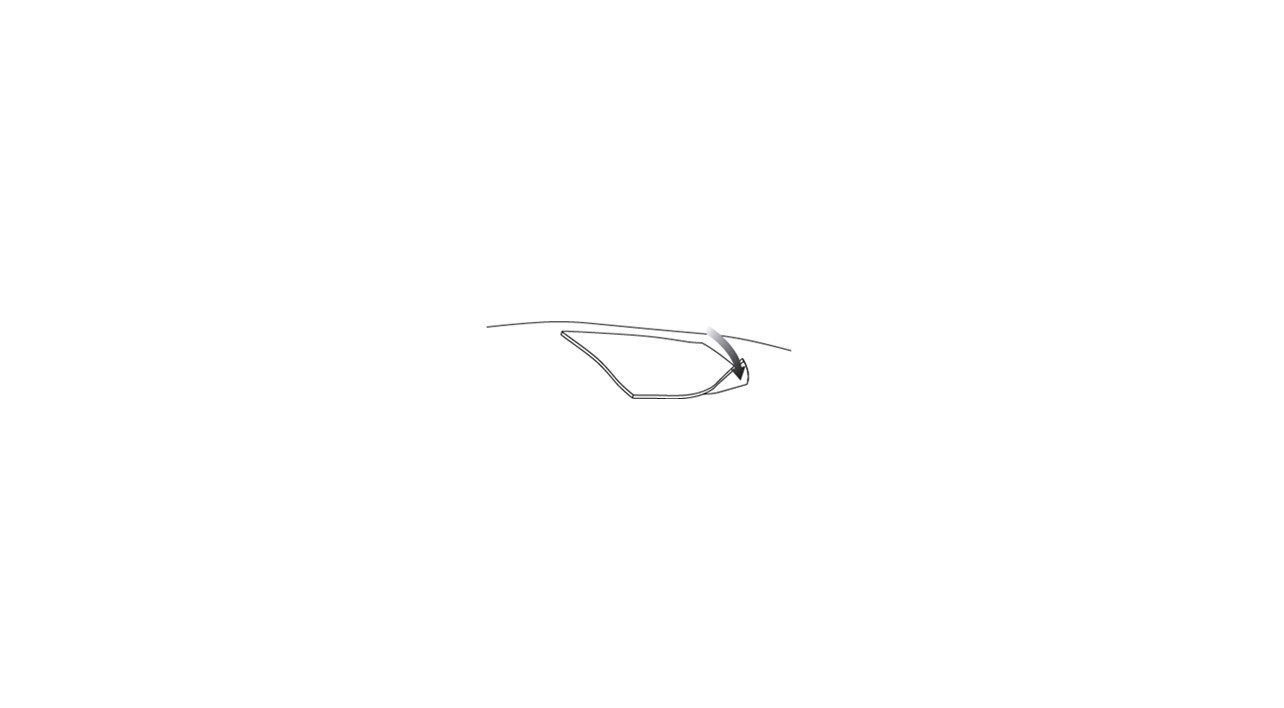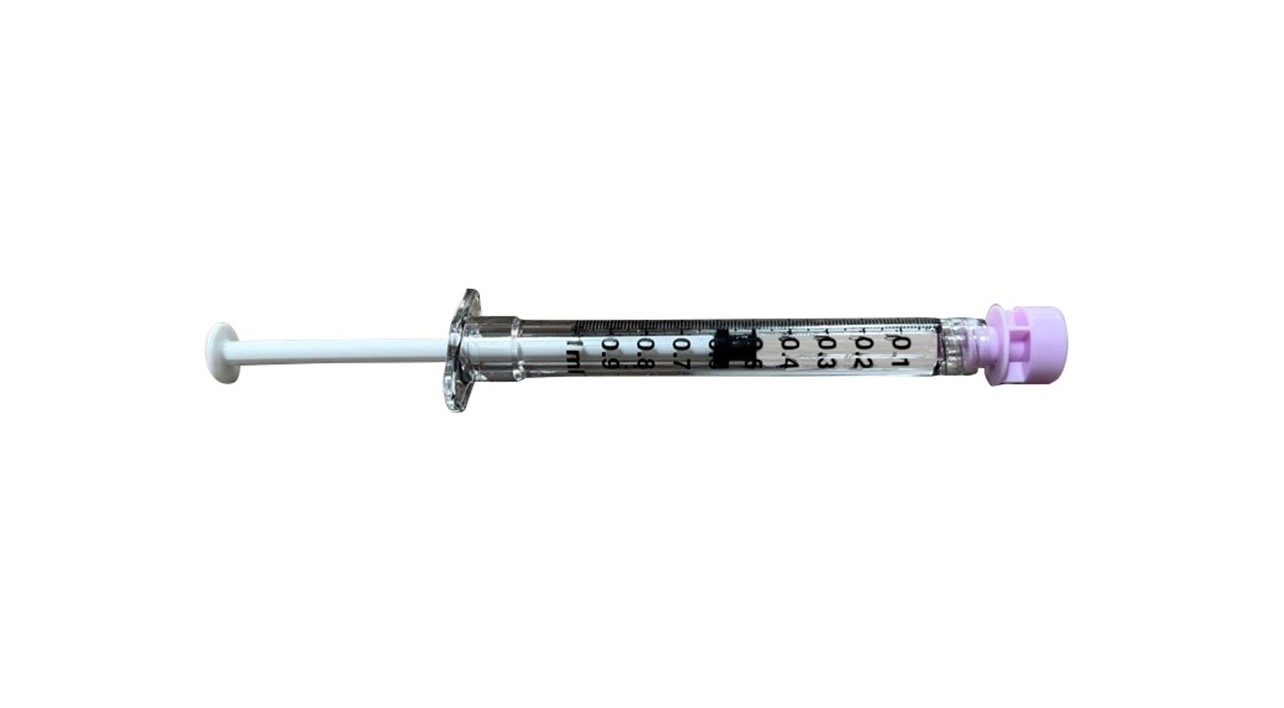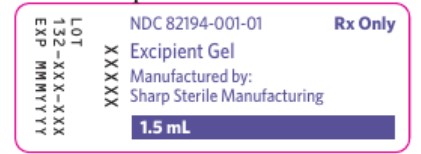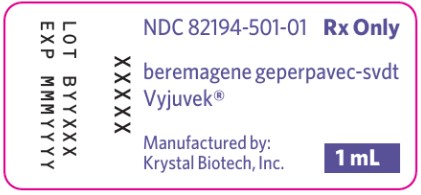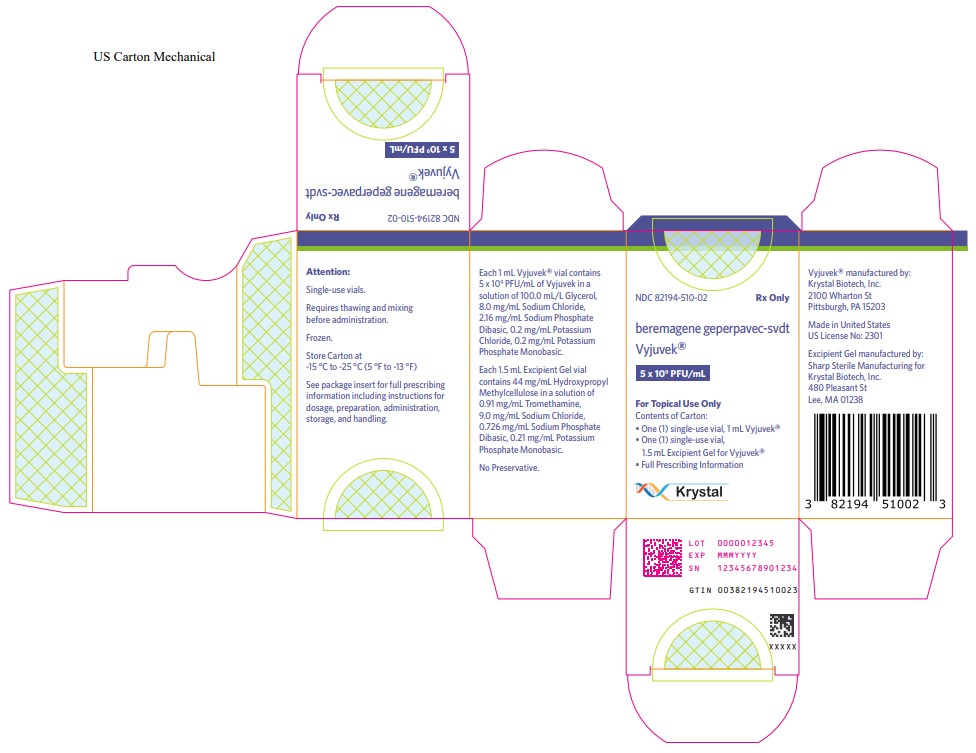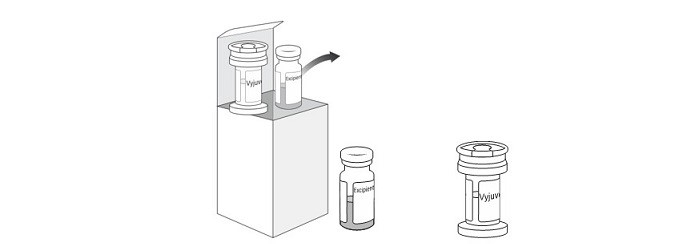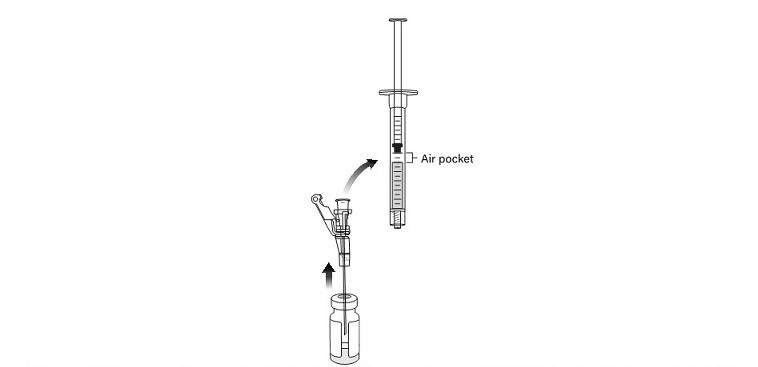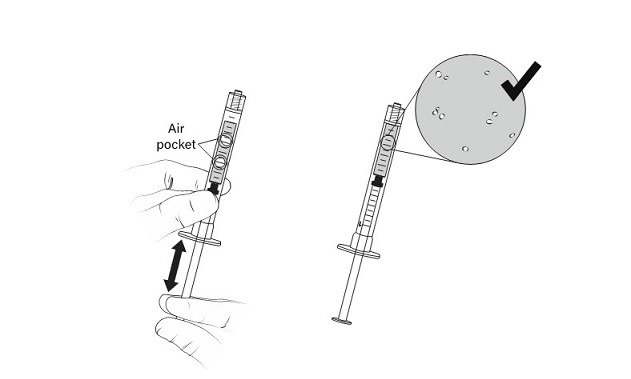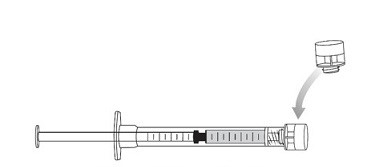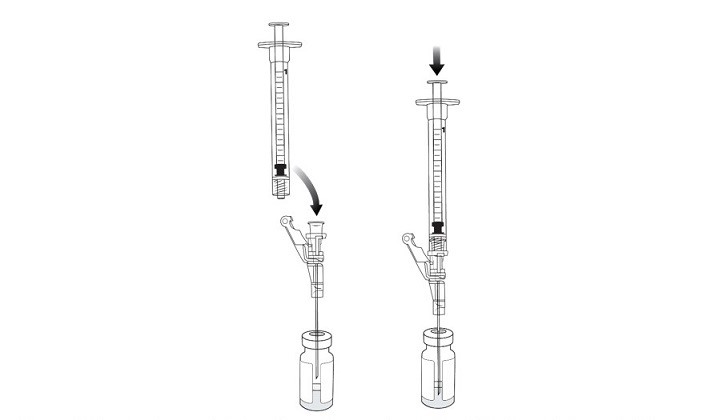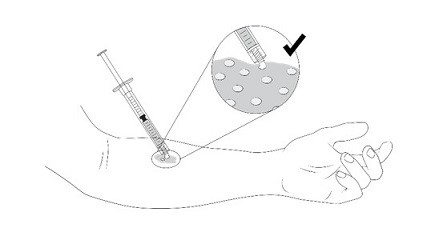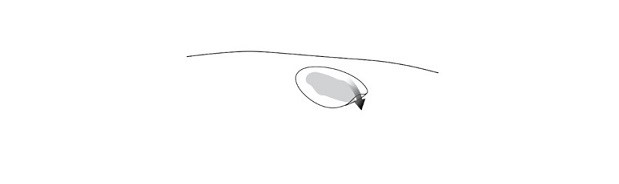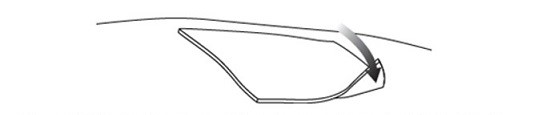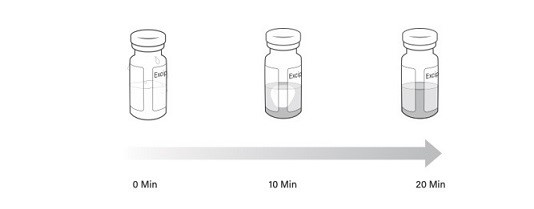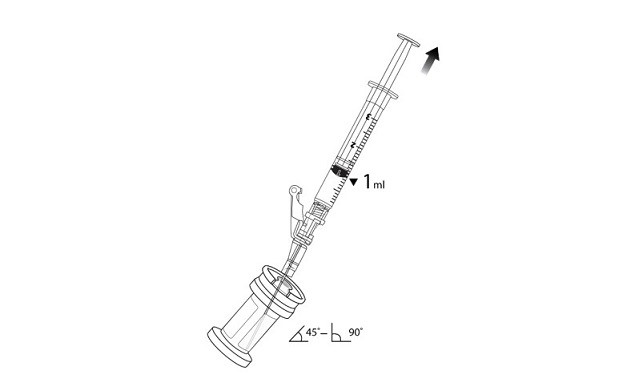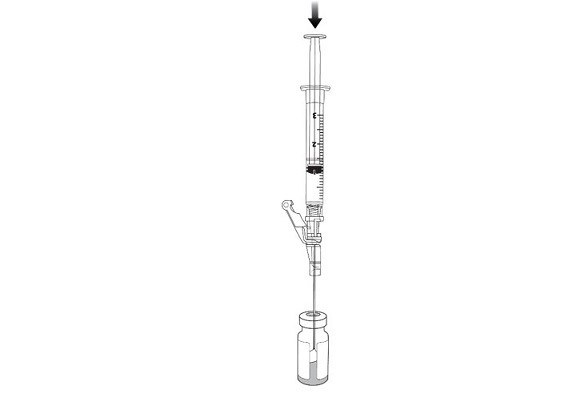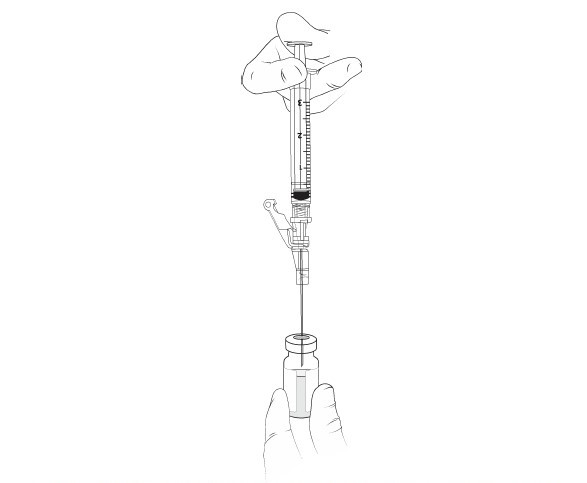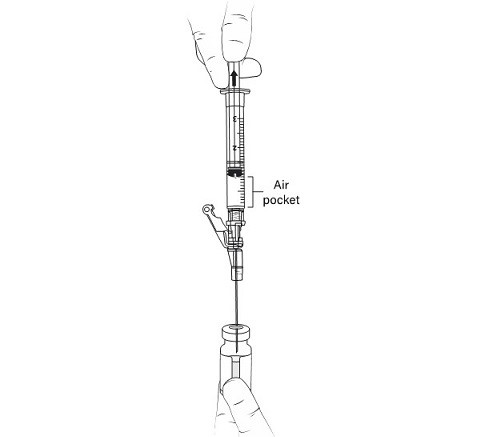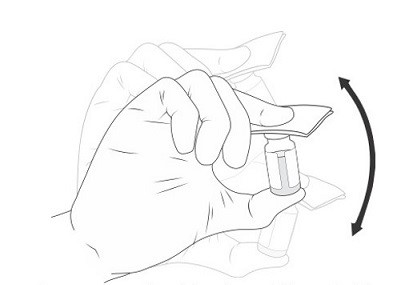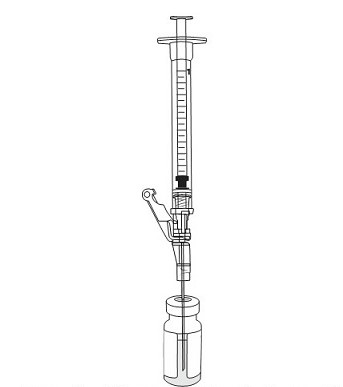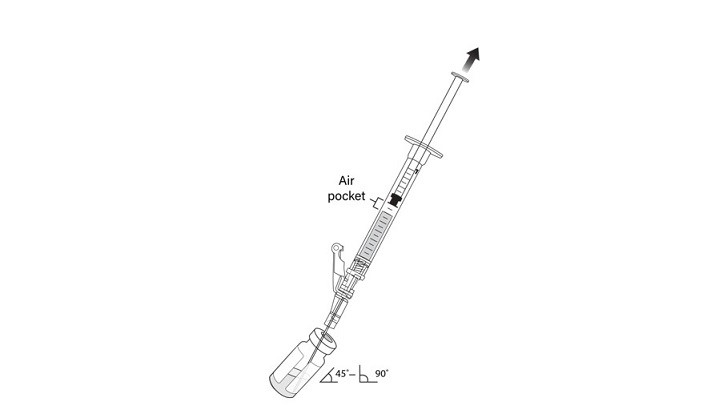 DRUG LABEL: VYJUVEK
NDC: 82194-510 | Form: KIT | Route: TOPICAL
Manufacturer: Krystal Biotech, Inc.
Category: prescription | Type: HUMAN PRESCRIPTION DRUG LABEL
Date: 20250929

ACTIVE INGREDIENTS: BEREMAGENE GEPERPAVEC 5000000000 [PFU]/1 mL
INACTIVE INGREDIENTS: GLYCERIN; SODIUM CHLORIDE; SODIUM PHOSPHATE DIBASIC DIHYDRATE; HYPROMELLOSE, UNSPECIFIED 1 mL/1 mL; TROMETHAMINE; SODIUM CHLORIDE; SODIUM PHOSPHATE DIBASIC DIHYDRATE; POTASSIUM PHOSPHATE, MONOBASIC

HIGHLIGHTS OF PRESCRIBING INFORMATION

These highlights do not include all the information needed to use VYJUVEK safely and effectively. See full prescribing information for
VYJUVEK.
VYJUVEK® (beremagene geperpavec-svdt) biological suspension mixedwith excipient gel for topical applicationInitial U.S. Approval: 2023

RECENT MAJOR CHANGES

Indications and Usage (1) | 09/2025
Dosage and Administration, Dose (2.1) | 09/2025

1 INDICATIONS AND USAGE

VYJUVEK is a herpes-simplex virus type 1 (HSV-1) vector-based gene therapy indicated for the treatment of wounds in adult and pediatric patients with dystrophic epidermolysis bullosa (DEB) with mutation(s) in the collagen type VII alpha 1 chain (COL7A1)gene. (1)

2 DOSAGE AND ADMINISTRATION

For topical application only.

Age Range | Maximum Weekly Dose (PFU) | Maximum Weekly Volume (mL)*
<3 years old | 2×10^9 | 1
≥3 years old | 4×10^9 | 2
PFU=plaque forming units; mL=milliliter
*Maximum weekly volume after mixing VYJUVEK biological suspension with excipient gel

Apply VYJUVEK gel to the selected wound(s) in droplets spaced evenly within the wound, approximately 1cm-by-1cm apart. (2.3)

- Apply VYJUVEK gel on wounds once a week. (2.1)
- See full prescribing information for instructions on preparation and handling, (2.2)and administration (2.3).

3 DOSAGE FORMS AND STRENGTHS

VYJUVEK is a biological suspension, mixed into excipient gel, for topical application. VYJUVEK biological suspension is supplied as a 1 mL extractable volume in a single dose vial at a nominal concentration of 5×10^9PFU/mL. The excipient gel is supplied as a 1.5 mL fill volume in a separate single use vial. VYJUVEK biological suspension (1 mL) is mixed into the excipient gel vial prior to administration as VYJUVEK gel. (3)

4 CONTRAINDICATIONS

None. (4)

5 WARNINGS AND PRECAUTIONS

- Accidental Exposure to VYJUVEK: Avoid direct contact with treated wounds and dressings of treated wounds until the next dressing change, following application. Clean the affected area if accidental exposure occurs. (5.1)

6 ADVERSE REACTIONS

The most common adverse drug reactions (incidence >5%) were itching, chills, redness, rash, cough, and runny nose. (6)

To report SUSPECTED ADVERSE REACTIONS, contact Krystal Biotech, Inc. at 1-844-557-9782 or FDA at 1-800-FDA-1088 or http://www.fda.gov/medwatch.

FULL PRESCRIBING INFORMATION

1 INDICATIONS AND USAGE

VYJUVEK is indicated for the treatment of wounds in adult and pediatric patients with dystrophic epidermolysis bullosa (DEB) with mutation(s) in the collagen type VII alpha 1 chain (COL7A1)gene.

2 DOSAGE AND ADMINISTRATION

2.1 Dose

For topical application on wounds only.

- The recommended dose of VYJUVEK gel is based on age (Table 1). VYJUVEK gel is applied topically to wound(s) once a week.

Table 1 Maximum Weekly Dose of VYJUVEK by Age
Age Range | Maximum Weekly Dose (PFU) | Maximum Weekly Volume (mL)*
<3 years old | 2×10^9 | 1
≥3 years old | 4×10^9 | 2
PFU=plaque forming unit; mL=milliliter
*Maximum weekly volume is the volume after mixing VYJUVEK biological suspension with excipient gel.

- It may not be possible to apply VYJUVEK gel to all the wounds at each treatment visit.
- Apply VYJUVEK gel to wounds until they are closed before selecting new wound(s) to treat.
- Prioritize weekly treatment to previously treated wounds if they re-open. [ see Administration (2.3)]
- If a dose is missed, apply VYJUVEK gel as soon as possible and resume weekly dosing thereafter.

2.2 Preparation

Important Preparation Instructions

- Prepare VYJUVEK gel at the pharmacy by mixing the VYJUVEK biological suspension into the excipient gel for immediate use. [see Storage and Handling (16.2)]
- The VYJUVEK gel prepared at the pharmacy, should be applied by a healthcare professional (HCP), patient, or caregiver either at a healthcare professional setting (e.g., clinic) or at a home setting.
- Individuals who are pregnant should not prepare or apply VYJUVEK gel and should avoid direct contact with the treated wounds or dressings from treated wounds [see Accidental Exposure to VYJUVEK(5.1)].

Below is the list of supplies needed for VYJUVEK gel preparation:

- One (1) carton containing one (1) VYJUVEK biological suspension vial and one (1) excipient gel vial (Figure 1)
- Two (2) 18-gauge needles
- Two (2) to four (4) 1 mL administration syringes
- One (1) 3 mL preparation syringe
- Two (2) to four (4) syringe caps
- Protective gloves
- 70% isopropyl alcohol pads
- Biohazard container
- Labels for administration syringes
- Virucidal agent for clean-up

Follow the steps below for VYJUVEK gel preparation.

PREPARE THE PREPARATION SYRINGE

1. Wash hands and put on protective gloves.
2. Remove both vials from the carton and thaw the VYJUVEK biological suspension vial and the excipient gel vial at room temperature for AT LEAST 20 minutes (Figure 1).

Figure 1 Carton containing the VYJUVEK biological suspension vial and excipient gel vial

Note: Visually inspect the vials to ensure both are in liquid form and completely thawed. Excipient gel is more viscous and will take longer to thaw (Figure 2).

Figure 2 Timelapse of excipient gel thaw from 0 minutes to 20 minutes

Note: Once either the VYJUVEK biological suspension or the excipient gel is thawed, do not refreeze.
3. Invert the VYJUVEK biological suspension vial 4-5 times. Do not invert the excipient gel vial.
4. Remove the caps from the vials and clean each vial stopper with a 70% isopropyl alcohol pad. Allow them to dry.
5. Aseptically connect an 18-gauge needle to the 3 mL preparation syringe.
6. Remove the needle cap and puncture the VYJUVEK biological suspension vial stopper.
7. Hold the vial at 45 to 90 degrees and withdraw 1 mL of VYJUVEK biological suspension into the preparation syringe (Figure 3).
8. Remove the preparation syringe (still connected to the needle) containing 1 mL of VYJUVEK biological suspension from the vial. Do NOT engage the safety lock.

Figure 3 The removal of 1 mL of biological suspension using the preparation syringe

9. Discard the VYJUVEK biological suspension vial in the biohazard waste.
10. Puncture the clean excipient gel stopper and transfer the VYJUVEK biological suspension into the excipient gel vial (Figure 4).

Figure 4 Transferring VYJUVEK biological suspension to excipient gel vial

11. WITHOUT REMOVING THE NEEDLE from the excipient gel vial, lift the tip of the needle above the liquid (Figure 5)and pull the plunger back to the 1 mL mark (Figure 6) to vent the gel vial following the addition of the 1 mL of suspension.

Figure 5 The needle above the liquid without removal of any material

Figure 6 Pulling the plunger back to the 1 mL mark to remove air pocket

12. Remove the preparation syringe with the 1 mL of air and engage the safety lock.
13. Discard the preparation syringe and needle into the biohazard waste.
14. Place a 70% isopropyl alcohol pad on top of the excipient gel stopper and hold it tightly in place.
15.Shake VIGOROUSLY for 10 SECONDS (Figure 7).

Figure 7 Manually mixing the excipient gel vial

Note: The mixture of VYJUVEK biological suspension and excipient gel is referred to as VYJUVEK gel.

PREPARE THE ADMINISTRATION SYRINGES
16. Aseptically connect an 18-gauge needle to the first 1 mL administration syringe and remove the needle cap.
17. Insert the 18-gauge needle into the excipient vial containing VYJUVEK gel (Figure 8).

Figure 8 Needle within VYJUVEK gel prior to withdraw

18. Tilt the vial 45 to 90 degrees and withdraw 0.5 mL of VYJUVEK gel (Figure 9).

Figure 9 Administration syringe withdrawing 0.5 mL of VYJUVEK gel with air pocket visible

Note: An air pocket may form near the plunger when extracting VYJUVEK gel.
19. DO NOT REMOVE THE NEEDLE FROM THE VIAL; lift the tip of the needle above the VYJUVEK gel and disconnect the administration syringe containing 0.5 mL of mixed VYJUVEK (Figure 10).

Figure 10 Disconnecting the administration syringe containing VYJUVEK gel with air pocket visible

Note: Leave the needle in the excipient gel vial stopper.
20. DO NOT flick the syringe to remove the air pocket. Manipulate the plunger up and down, until all air pockets have been removed (Figure 11)

Figure 11 Manipulation of administration syringe plunger to remove air pockets

21. Cap the administration syringe and set aside (Figure 12).

Figure 12 Capped syringe

22. Connect a new 1 mL administration syringe to the needle that remains in the excipient gel vial stopper (with the tip of the needle ABOVE the VYJUVEK gel) (Figure 13).

Figure 13 Connecting an administration syringe to the needle within the excipient gel vial stopper

23. Place the bevel of the needle in the VYJUVEK gel, tilt the vial 45 to 90 degrees and withdraw 0.5 mL of VYJUVEK gel into the administration syringe [see steps 17 and 18: Figure 8 and Figure 9)].
24. Complete steps 19, 20, and 21 above to disconnect the administration syringe and remove the air pockets, prior to capping the administration syringe (Figure 10, Figure 11, and Figure 12).
25. Repeat steps 22, 23, and 24 if two (2) additional administration syringes are required (each containing 0.5 mL of VYJUVEK gel).
Note: Administration syringes are labeled as syringe #1, #2, #3, and #4.
26. Discard the excipient gel vial (with the needle within the vial stopper) into the biohazard container.
27. Clean all surfaces that may have come in contact with VYJUVEK biological suspension or gel and treat all spills with a virucidal agent such as 70% isopropyl alcohol, 6% hydrogen peroxide, or <0.4% ammonium chloride. Blot using absorbent materials.
28. Dispose all materials (e.g., vial, syringe, needle, cleaning materials) that may have come in contact with VYJUVEK biological suspension or gel into a biohazard container.
29. Place the capped administration syringes containing the VYJUVEK gel in a sealable plastic bag.
30. Place the sealable plastic bag with administration syringes into an appropriate insulated or temperature regulated secondary container at 2° to 8°C (35.6° to 46.4°F) for transport from the preparation site to the administration site.

2.3 Administration

Below is the list of supplies needed for VYJUVEK gel administration:

- The administration syringes
- Hydrophobic dressing
- Scissors
- Standard dressing
- Protective gloves
- Biohazard container
- Virucidal agent for clean-up

VYJUVEK GEL ADMINISTRATION

Note: The administration syringe should be primed prior to the initial application by pulling the plunger down and pushing it upwards, so that a small droplet of VYJUVEK gel forms at the tip of the syringe.

Follow the steps below for VYJUVEK gel administration.

1. Apply VYJUVEK gel to the selected wound(s) in droplets spaced evenly within the wound, approximately 1cm-by-1cm apart (width of a fingertip). The resulting droplet pattern should loosely resemble a grid. Avoid touching the administration syringe to the skin and/or wound (Figure 14).

Figure 14 Application of VYJUVEK gel to the wound

Table 2below provides a reference on dose per approximate size of the wound.

Dose by Wound Size

Wound Area (cm^2) | Dose (PFU) | Volume (mL)
< 20 | 4×10^8 | 0.2
20 to < 40 | 8×10^8 | 0.4
40 to 60 | 1.2×10^9 | 0.6
PFU= plaque forming unit; mL= milliliter; cm= centimeter
* For wound area over 60 cm^2, recommend calculating the total dose based on Table 2 until the maximum weekly dose in Table 1 is reached.

2. Use the clean scissors to cut the hydrophobic dressing to a size slightly larger than the wound and place the dressing atop the VYJUVEK gel droplets (Figure 15).

Figure 15 Placing the hydrophobic dressing over the treated wound

3. Use the scissors to cut the standard dressing used by the patient to a size slightly larger than the hydrophobic dressing and place the standard dressing atop the hydrophobic dressing (Figure 16).

Figure 16 Placing the standard dressing over the hydrophobic dressing

4. Clean all surfaces that may have come in contact with VYJUVEK gel and treat all spills with a virucidal agent such as 70% isopropyl alcohol, 6% hydrogen peroxide or <0.4% ammonium chloride. Blot using absorbent materials.
5. Dispose all materials (e.g., syringe, cleaning materials) that may have come in contact with VYJUVEK biological suspension or gel into a biohazard container.
6. Discard unused administration syringes containing the VYJUVEK gel after preparation into a biohazard container [ see Storage and Handling (16.2)] .
7. The dressing should be left in place until the next dressing change after VYJUVEK gel application. Once the VYJUVEK dressings are removed, the patient may continue with their standard of care.

3 DOSAGE FORMS AND STRENGTHS

VYJUVEK is an opalescent yellow to colorless biological suspension, mixed into excipient gel, for topical application. VYJUVEK biological suspension is supplied as a 1 mL extractable volume in a single-use vial with a green cap, at a nominal concentration of 5×10^9PFU/mL. The excipient gel is a clear viscous solution supplied as a 1.5 mL fill volume in a separate single-use vial with a blue cap.

VYJUVEK biological suspension (1 mL) is mixed into the excipient gel vial prior to administration.

4 CONTRAINDICATIONS

None.

5 WARNINGS AND PRECAUTIONS

5.1 Accidental Exposure to VYJUVEK

Accidental exposure to VYJUVEK may occur to close contacts and caregivers. VYJUVEK is a genetically modified, herpes-simplex virus type 1 vector-based, replication-deficient, non-integrating gene therapy. VYJUVEK will not replicate in the patient’s cells and does not integrate into the patient cells’ native genetic material. For precautions,

- Avoid direct contact with treated wounds (e.g., touching or scratching) and dressings of treated wounds until the next dressing change.
- Wear protective gloves when assisting patients with changing wound dressings and handling the disposal.
- In the event of an accidental exposure through a splash to the eyes or mucous membranes, flush with clean water for at least 15 minutes.

6 ADVERSE REACTIONS

The most common adverse reactions (>5%) were itching, chills, redness, rash, cough, and runny nose.

6.1 Clinical Trials Experience

Because clinical trials are conducted under widely varying conditions, adverse reaction rates observed in the clinical trials of a drug cannot be directly compared to rates in the clinical trials of another drug and may not reflect the rates observed in practice.

The safety data described in this section reflects exposure to VYJUVEK gel in a randomized, intra-patient placebo‑controlled study. A total of 31 patients with dystrophic epidermolysis bullosa (DEB), including 30 patients with autosomal recessive DEB and one patient with autosomal dominant DEB received topical administration of VYJUVEK gel to their wounds. The age of the patients ranged from 1 year to 44 years (mean age 17 years). Of the 31 patients, 19 (61%) were pediatric patients (less than 17 years of age), and 11 (36%) were females. Each patient received weekly topical application of VYJUVEK gel at one or more wound sites and placebo at a matching wound site as an intra-subject comparator. The median duration of exposure to VYJUVEK gel was 25 weeks. The most frequent adverse reactions (incidence >5%) observed in the study are summarized in Table 3. There were no discontinuations due to adverse reactions.

Table 3Adverse Reactions (incidence >5%) Following Treatment with VYJUVEK gel (n =31)

Adverse Reactions | Patients n (%)
Itching | 3 (10)
Chills | 3 (10)
Redness | 2 (6)
Rash | 2 (6)
Cough | 2 (6)
Runny Nose | 2 (6)

In addition, the safety profile of VYJUVEK in two patients with autosomal recessive DEB (RDEB) of six and seven months of age, respectively, who received topical VYJUVEK gel weekly in an open-label study was similar to the safety profile of VYJUVEK observed in the randomized, intra-patient placebo‑controlled study described above.

7 DRUG INTERACTIONS

No drug interaction studies have been performed.

8 USE IN SPECIFIC POPULATIONS

8.1 Pregnancy

Risk Summary

There are no data with VYJUVEK gel use in pregnant women to inform a drug-associated risk. Animal developmental and reproductive toxicity studies have not been conducted with VYJUVEK.

The estimated background risk of major birth defects and miscarriage for the indicated population is unknown. In the U.S. general population, the estimated background risks of major birth defects and miscarriage in clinically recognized pregnancies is 2-4% and 15-20%, respectively.

Clinical Considerations

If the patient becomes pregnant while being administered VYJUVEK gel, the patient should be apprised of the potential hazards to the fetus and neonate. Women of childbearing potential should be advised to use an effective method of contraception to prevent pregnancy during treatment with VYJUVEK gel.

8.2 Lactation

Risk Summary

There is no information available on the presence of VYJUVEK in human milk, the effects on the breastfed infant, or the effects on milk production. Animal lactation studies have not been conducted with VYJUVEK.

The developmental and health benefits of breastfeeding should be considered along with the mother’s clinical need for VYJUVEK and any potential adverse effects on the breastfed child from VYJUVEK or from the underlying maternal condition.

8.3 Females and Males of Reproductive Potential

No nonclinical or clinical studies were performed to evaluate the effect of VYJUVEK on fertility.

8.4 Pediatric Use

The safety and effectiveness of VYJUVEK have been established in pediatric patients with dystrophic epidermolysis bullosa (DEB). The use in pediatric patients (0 to 16 years of age) was supported by evidence from adequate and well-controlled study which included 19 pediatric patients 1 year of age and older. [ see Adverse Reactions (6) Clinical Studies (14)].

8.5 Geriatric Use

Clinical study of VYJUVEK gel did not include geriatric patients aged 65 years and older.

11 DESCRIPTION

VYJUVEK (beremagene geperpavec-svdt) is a suspension of an HSV-1 vector-based gene therapy, mixed with the supplied sterile excipient gel for topical application on wounds. VYJUVEK is a live, replication defective HSV-1-based vector that has been genetically modified to express the human type VII collagen (COL7) protein. The parental virus for VYJUVEK was a primary isolate, which was subsequently altered using recombinant methods to result in gene deletions and insertions.

VYJUVEK is an opalescent yellow to colorless biological suspension following thaw from its frozen state. Each 1 mL VYJUVEK vial contains 5×10^9PFU/mL of VYJUVEK in a solution of 100.0 mL/L Glycerol, 8.0 mg/mL Sodium Chloride, 2.16 mg/mL Sodium Phosphate Dibasic, 0.2 mg/mL Potassium Chloride, 0.2 mg/mL Potassium Phosphate Monobasic.

The excipient gel is a clear viscous solution, following thaw from its frozen state. Each 1.5 mL Excipient Gel vial contains 44 mg/mL Hydroxypropyl Methylcellulose in a solution of 0.91 mg/mL Tromethamine, 9.0 mg/mL Sodium Chloride, 0.726 mg/mL Sodium Phosphate Dibasic, 0.21 mg/mL Potassium Phosphate Monobasic.

VYJUVEK biological suspension is mixed into excipient gel prior to administration. After mixing, VYJUVEK gel consists of 5×10^9PFU in a volume of 2.5 mL.

Neither VYJUVEK biological suspension nor the excipient gel contains preservatives.

12 CLINICAL PHARMACOLOGY

12.1 Mechanism of Action

Dystrophic epidermolysis bullosa (DEB) is caused by mutation(s) in the COL7A1gene, which results in reduced or absent levels of biologically active COL7.

Upon topical application to the wounds, VYJUVEK can transduce both keratinocytes and fibroblasts. Following entry of VYJUVEK into the cells, the vector genome is deposited in the nucleus. Once in the nucleus, transcription of the encoded human COL7A1is initiated. The resulting transcripts allow for production and secretion of COL7 by the cell in its mature form. These COL7 molecules arrange themselves into long, thin bundles that form anchoring fibrils. The anchoring fibrils hold the epidermis and dermis together and are essential for maintaining the integrity of the skin. Patients with autosomal dominant DEB (DDEB) have lower than normal functional anchoring fibrils, and patients with RDEB have no functional anchoring fibrils.

12.2 Pharmacodynamics

The pharmacodynamic activity (expression and localization of COL7 transgene) of VYJUVEK gel was demonstrated in an initial clinical study (n=6 patients). Linear deposition of the non-collagenous domain 1 (NC1) and domain 2 (NC2) of COL7 were observed at the dermal-epidermal junction in skin biopsies harvested after VYJUVEK treatment.

12.3 Pharmacokinetics

In an initial clinical study, viral vector DNA was detected in skin swab samples in all nine treated patients, with maximum level ranging from 5.1×10^4to 4.1×10^8vector genomes. In 6 out of 9 patients (67%), negative shedding was confirmed with three measurements below limit of detection within 8 weeks of treatment with VYJUVEK. No viral vector DNA was detected in blood or urine.

In the 31-patient randomized, double-blind, intra-patient placebo-controlled trial, systemic and potential environmental exposure assessments were conducted at weekly clinical site visits via quantification of VYJUVEK genomes in blood, urine, skin swabs, and bandage samples (vector shedding) using a validated qPCR assay, and detection of infectious viral particles in skin swabs (infectivity) using a validated plaque titer assay.

All blood samples and all but one urine sample collected throughout the study were below the limit of detection. Skin swabs from 19 of the 31 patients (61%) were positive for viral vector following treatment with VYJUVEK. Negative shedding from skin swabs was achieved in 16 of the 19 patients (84%) within six weeks following treatment with VYJUVEK. Most wound dressings (94%, 29/31) contained a range of detectable vector genomes. However, no extracellular infectious particles were detected on the skin surface of any patient at any timepoint tested, after topical VYJUVEK application.

12.6 Immunogenicity

There was minimum potential for systemic exposure to VYJUVEK. Antibodies against the viral vector (HSV-1) and transgene protein (COL7) were evaluated in a subset of patients in the randomized, intra-patient placebo-‑controlled clinical study. A total of 64% of evaluated patients (14/22) were anti-HSV-1 antibody positive at baseline. Six of the 8 anti-HSV-1 seronegative patients seroconverted by Week 26 following treatment with VYJUVEK. For patients with available matched baseline and end-of-study serum samples, anti‑drug antibodies (ADAs) to COL7 were detected in 72% (13/18) of patients treated with VYJUVEK for up to 26 weeks. Data are limited to perform correlative assessment on the impact of ADA on pharmacodynamic activity.

13 NONCLINICAL TOXICOLOGY

13.1 Carcinogenesis, Mutagenesis, Impairment of Fertility

No animal studies have been conducted to evaluate the effects of VYJUVEK on carcinogenesis, mutagenesis, or impairment of fertility.

14 CLINICAL STUDIES

The efficacy of VYJUVEK gel was evaluated in one randomized, double-blind, intra-patient placebo-controlled study (NCT04491604). The study enrolled patients with dystrophic epidermolysis bullosa (DEB) with genetically confirmed mutation(s) in the COL7A1 gene and who had two cutaneous wounds with similar size, appearance, and anatomical location. Two comparable wounds in each patient were selected and randomized to receive either topical application of VYJUVEK gel or the placebo (excipient gel) weekly for 26 weeks..

A total of 31 patients were treated with VYJUVEK and placebo. The demographic characteristics of the population were as follows: the mean age was 17 years (range 1 to 44 years) including 19 pediatric patients (aged 1 to 16 years), 20 patients (65%) were male, 20 patients (65%) were White, 6 patients (19%) were Asian, and 5 patients (16%) were American Indian or Alaskan Native. Thirty patients had autosomal recessive DEB
and one patient had autosomal dominant DEB. The size of the VYJUVEK gel-treated wounds ranged from 2 to 57 cm^2, with 74% of wounds < 20 cm^2and 19% from 20 to < 40 cm^2. The size of the placebo gel-treated wounds ranged from 2 to 52 cm^2, with 71% of wounds < 20 cm^2 and 26% from 20 to < 40 cm^2.

Primary efficacy outcome measure was improved wound healing defined as the difference in the proportion of complete (100%) wound closure at 24 Weeks confirmed at two consecutive study visits 2 weeks apart, assessed at Weeks 22 and 24 or at Weeks 24 and 26, between the VYJUVEK gel-treated and the placebo gel-treated wounds. Other efficacy outcome measures were the difference in the proportion of complete wound closure assessed at Weeks 8 and 10 or at Weeks 10 and 12 between the VYJUVEK gel-treated and the placebo gel-treated wounds. Complete (100%) wound closure was defined as durable wound closure evaluated at two consecutive visits two weeks apart. The efficacy results are summarized in Table 4.

Table 4Summary of the efficacy results for VYJUVEK gel

Wound Closure Assessment Timepoints | Complete Wound Closure,; n (%); VYJUVEK gel; (N=31) | Complete Wound Closure,; n (%); Placebo gel; (N=31) | Treatment Difference; (95% CI) | p value
Weeks 22 & 24 or Weeks 24 & 26 | 20 (65) | 8 (26) | 39%; (14, 63) | 0.012
Weeks 8 & 10 or Weeks 10 & 12 | 21 (68) | 7 (23) | 45%; (22, 69) | 0.003

16 HOW SUPPLIED/ STORAGE AND HANDLING

16.1 How Supplied

Each carton of VYJUVEK (NDC 82194-510-02) contains one single-dose vial of VYJUVEK biological suspension and one single-dose vial of excipient gel.

VYJUVEK biological suspension (inner NDC 82194-501-01), green cap, is supplied as a 1 mL extractable volume in a single-use, single-dose vial containing 5×10^9PFU/mL.

Excipient gel (inner NDC 82194-001-01), blue cap, is supplied as a 1.5 mL fill volume in a separate single-use, single-dose vial.

16.2 Storage and Handling

Store the VYJUVEK carton in the pharmacy at -15°C to -25°C (5°F to -13°F). If a freezer is not available, the carton can be refrigerated in the pharmacy (2° to 8°C (35.6° to 46.4°F)) for up to 1 month.

Prior to use, VYJUVEK requires mixing into excipient gel in the pharmacy.

Administration syringes containing the VYJUVEK gel may remain at room temperature (20 to 25°C (68° to 77°F)) for up to 8 hours prior to application. If immediate use is not possible, administration syringes can be kept in an appropriate insulated or temperature regulated secondary container for up to 48 hours at 2° to 8°C (35.6° to 46.4°F).

Discard material if it falls out of the parameters described above.

VYJUVEK is a replication deficient HSV-1-based gene therapy. See Dosage and Administration (2)for appropriate handling, preparation, application, and disposal of materials. Follow universal biohazard precautions for handling.

17 PATIENT COUNSELING INFORMATION

Advise the patient or caregiverto read the FDA-approved patient labeling (Medication Guide and Instructions for Use).

Advise patients and caregivers of the following precautions prior to and during treatment with VYJUVEK gel:

- Avoid direct contact with treated wounds (e.g., touching and scratching) and dressings of treated wounds until the next dressing change following VYJUVEK gel application. In the event of accidental exposure, instruct patients and exposed individuals to clean the affected area [see Warnings and Precautions (5.1)].
- Wash hands and wear protective gloves when changing wound dressings [see Preparation (2.2)].
- Disinfect bandages from the first dressing change with a virucidal agent, such as 70% isopropyl alcohol, 6% hydrogen peroxide, or <0.4% ammonium chloride, and dispose of the disinfected bandages in a separate sealed plastic bag in household waste. Dispose of the subsequent used dressings and cleaning materials into a sealed plastic bag and dispose in household waste [see Administration (2.3)].

Manufactured by:
Krystal Biotech, Inc.
2100 Wharton Street, Suite 701
Pittsburgh, PA 15203
U.S. License No. 2301

VYJUVEK® is a registered trademark of Krystal Biotech, Inc.

© 2025 Krystal Biotech, Inc. All rights reserved.

MEDICATION GUIDE VYJUVEK (vye-JOO-vek) Gel (beremagene geperpavec-svdt) biological suspension mixed with excipient gel, for topical use

MEDICATION GUIDE

VYJUVEK (Vye-JOO-vek) Gel

(beremagene geperpavec-svdt)

biological suspension mixed with gel, for topical use

What is the most important information I should know about VYJUVEK Gel?
…The VYJUVEK® biological suspension must be mixed with the gel at the pharmacy prior to use.
…VYJUVEK gel should be applied by a healthcare professional (HCP) or by a patient/caregiver either at a healthcare professional setting (e.g., clinical) or a home setting.

What is VYJUVEK Gel?
…VYJUVEK gel is a prescription medicine for the treatment of wounds (topical use only), in adult and pediatric patients who have dominant or recessive dystrophic epidermolysis bullosa.

Who should not take VYJUVEK Gel?
… Individuals who are pregnant should not prepare or apply VYJUVEK gel and should avoid direct contact with the treated wounds or dressings from treated wounds.

Before taking VYJUVEK Gel, tell your healthcare provider about all of your medical conditions, including if you:
… are pregnant or plan to become pregnant. It is not known if VYJUVEK gel will harm your unborn baby.
…are breast feeding or plan to breast feed. It is not known if VYJUVEK gel passes into your breast milk.
Tell your doctor about all the medicines you take, including prescription and over-the-counter medicines, vitamins, and herbal supplements.

How should I take VYJUVEK Gel?
…See the Instructions For Use for detailed instructions.
…Use VYJUVEK exactly as your healthcare providers tells you to and do not use past the expiration date. If you have questions, reach out to your provider or the pharmacy for further instructions.

What should I avoid while taking VYJUVEK Gel?
…Avoid direct contact with treated wounds (e.g., touching or scratching) and dressings of treated wounds until the next dressing change following VYJUVEK gel application.
…Individuals should wear protective gloves when assisting with changing wound dressings and handling the disposal of the dressings.

What are the possible side effects of VYJUVEK Gel?
…The most common side effects of VYJUVEK gel are itching, chills, redness, rash, cough, and runny nose.

Call your doctor for medical advice about side effects. You may report side effects to FDA at 1-800-FDA-1088.

How should I store VYJUVEK Gel?
…See the Instructions For Use for detailed instructions.
…VYJUVEK gel syringes may remain at room temperature (20° to 25°C (68° to 77°F)) for up to 8 hours prior to application. Administration syringes can be kept in an appropriate insulated or temperature regulated secondary container for up to 48 hours at 2° to 8°C (35.6° to 46.4°F).
…Follow expiration information provided by the pharmacy. If you have any questions, reach out to the pharmacy for additional information.

General information about the safe and effective use of VYJUVEK Gel
…Medicines are sometimes prescribed for purposes other than those listed in a Medication Guide. Do not use VYJUVEK gel for a condition for which it was not prescribed. Do not give VYJUVEK gel to other people, even if they have the same symptoms that you have. It may harm them.
…You can ask your pharmacist or healthcare provider for information about VYJUVEK gel that is written for health professionals.

What are the ingredients in VYJUVEK Gel?
Active ingredients: beremagene geperpavec-svdt

Inactive ingredients: glycerol, sodium chloride, sodium phosphate dibasic, potassium chloride, potassium phosphate monobasic, hydroxypropyl methylcellulose, and tromethamine

Manufactured by: Krystal Biotech, Inc.
2100 Wharton Street, Suite 701
Pittsburgh, PA 15203
U.S. License No. 2301

For more information, go to www.vyjuvek.com or call 1-844-5-KRYSTAL (1-844-5-579-7825)

This Medication Guide has been approved by the U.S. Food and Drug Administration. Revised: 09/2025

INSTRUCTIONS FOR USE VYJUVEK (vye-JOO-vek) Gel (beremagene geperpavec-svdt) biological suspension mixed with excipient gel, for topical use

This Instructions for Use contains information on how to apply VYJUVEK gel.

Read the Instructions for Use before you start using VYJUVEK gel. This information does not take the place of talking to your healthcare provider about your medical condition or your treatment.

You or your caregiver should be shown how to apply VYJUVEK gel before the first use.

Vyjuvek Gel Syringe

Important Information You Need to Know Before Applying VYJUVEK Gel

Before Starting VYJUVEK GelIndividuals who are pregnant or nursing should not prepare or apply VYJUVEK gel and should avoid direct contact with the treated wounds or dressings from treated wounds, as this has not been formally studied. It is important to tell your healthcare provider if you are breastfeeding or plan to do so. They will then help you decide whether to stop breast-feeding, or whether to stop taking VYJUVEK gel, taking into account the benefit of breast-feeding to the baby and the benefit of VYJUVEK gel to you.

If you are allergic to beremagene geperpavec-svdt or any of its ingredients, you should not be given VYJUVEK gel.

Tell your healthcare provider about your standard of care routine including medications (prescribed and over the counter), bathing routine, dressing use, etc. before starting VYJUVEK gel.

How is VYJUVEK Gel Supplied?
Syringes containing VYJUVEK gel will be provided by the pharmacy in a sealable plastic bag. VYJUVEK gel in the syringes is ready for administration.

Measures for Accidental Exposure
To avoid accidental exposure follow the below instructions for the administration and handling of VYJUVEK gel:

- Wash hands and wear protective gloves while administering VYJUVEK gel.
- In the event of an accidental exposure through a splash to the eyes or mouth, flush with clean water for at least 15 minutes.
- Avoid direct contact with treated wounds (e.g., touching or scratching) and dressings of treated wounds until the next dressing change.
- Disinfect bandages from the first dressing change with a virucidal agent, such as 70% isopropyl alcohol, 6% hydrogen peroxide, or <0.4% ammonium chloride, and dispose of the disinfected bandages in a separate sealed plastic bag in household waste.

Storing VYJUVEK Gel Syringes
Follow the instructions provided by the pharmacy and do not use the syringes past their expiration.

- VYJUVEK gel syringes are provided by the pharmacy in a refrigerated (2° to 8°C (35.6° to 46.4°F)) container.
- VYJUVEK gel syringes can be stored at room temperature (20 to 25°C (68° to 77°F)) for up to 8 hours prior to application. Administration syringes can be kept in an appropriate insulated or temperature regulated secondary container for up to 48 hours at 2° to 8°C (35.6° to 46.4°F).
- Store VYJUVEK gel syringes out of the reach of children.
- Do NOT heat the syringes or place them in the microwave.

Applying VYJUVEK Gel
Work with your healthcare provider to determine the best wound preparation, administration and dressing routine that works for you.

It may not be possible to treat all wounds each week. VYJUVEK gel should be applied to wounds until they are closed before selecting new wound(s) to treat. Weekly treatment of previously treated wounds should be prioritized if they re-open.

If a dose is missed, VYJUVEK gel should be administered as soon as possible, and weekly treatments will continue. It is not recommended to stop your treatment without first consulting your doctor or nurse.

Wound Preparation
The wounds should be clean before applying VYJUVEK gel.

- Gently remove any medicines, ointments, drainage, scabbing, and dead skin at the wound area.
-
  - Bathing is not required.
- Leaving wounds uncovered can be painful to some patients. Ensure your area is set-up and ready prior to beginning application.
-
  - In some cases, it may be best to keep wounds covered and treat one area at a time, removing dressings as you go.
- Do not use products or dressing that may contain anti-viral agents within 24 hours prior to use of VYJUVEK gel.
-
  - If you are unsure if a product contains an anti-viral agent, refer to the Manufacturer’s website at the end of this document for more information or contact your healthcare provider on what to avoid.

Supplies

Below is the list of supplies needed for VYJUVEK gel administration:

- VYJUVEK gel syringes
- Hydrophobic dressing
  - Refer to the Manufacturer’s website at the end of this document or contact your healthcare provider for more information on hydrophobic dressing options.
- Clean scissors
- Standard dressing
- Gloves
- Biohazard container
- Virucidal agent and absorbent material for clean-up

Follow the steps below for VYJUVEK gel administration.

The administration syringe should be primed prior to the initial application by pulling the plunger down and gently pushing it upwards, so that a small droplet of VYJUVEK gel forms at the tip of the syringe.

Step 1.Apply VYJUVEK gel to the selected wound(s) in droplets spaced evenly within the wound, approximately 1 cm-by-1 cm apart (width of a fingertip). The resulting droplet pattern should loosely resemble a grid. Avoid touching the administration syringe directly to the wound, only the droplet will touch the wound (Figure 1).

Note:You can treat the wound underneath the blister cap after it has been drained. Additionally, the VYJUVEK gel can be applied directly to the hydrophobic dressing in the same 1 cm-by-1 cm pattern to the size of the wound, if direct administration is difficult.

Figure 1 Application of VYJUVEK gel to the wound

Step 2.Use the scissors to cut the hydrophobic dressing to a size slightly larger than the wound and place the dressing atop the VYJUVEK gel droplets (Figure 2).

Figure 2 Placing the hydrophobic dressing over the treated wound

Step 3.Use the scissors to cut the standard dressing to a size slightly larger than the hydrophobic dressing and place the standard dressing atop the hydrophobic dressing (Figure 3).

Figure 3 Placing the standard dressing over the hydrophobic dressing

Step 4.The VYJUVEK gel dressing should be left in place until the next dressing change. Disinfect VYJUVEK gel dressings, place in a sealable bag and discard into the household waste. Continue with your standard of care routine.

Disposal and Clean-up of VYJUVEK Gel
Clean all surfaces that may have come in contact with VYJUVEK gel and treat all spills (blot using absorbent material) with a virucidal agent such as 70% isopropyl alcohol, 6% hydrogen peroxide, or <0.4% ammonium chloride.

Dispose all materials (e.g., used and unused syringe (expired), cleaning materials) that may have come in contact with VYJUVEK gel into a biohazard container.

Once the VYJUVEK gel dressings are removed and disinfected with a virucidal agent, place them in a sealable bag and discard into the household waste. Standard of care routine can then be continued.

Additional Information

Manufactured by: Krystal Biotech, Inc.
2100 Wharton Street, Suite 701
Pittsburgh, PA 15203
U.S. License No. 2301

For more information, go to www.vyjuvek.com or call 1-844-5-KRYSTAL (1-844-5-579-7825)

This “Instructions for Use” has been approved by the U.S. Food and Drug Administration.

Approved: September 2025